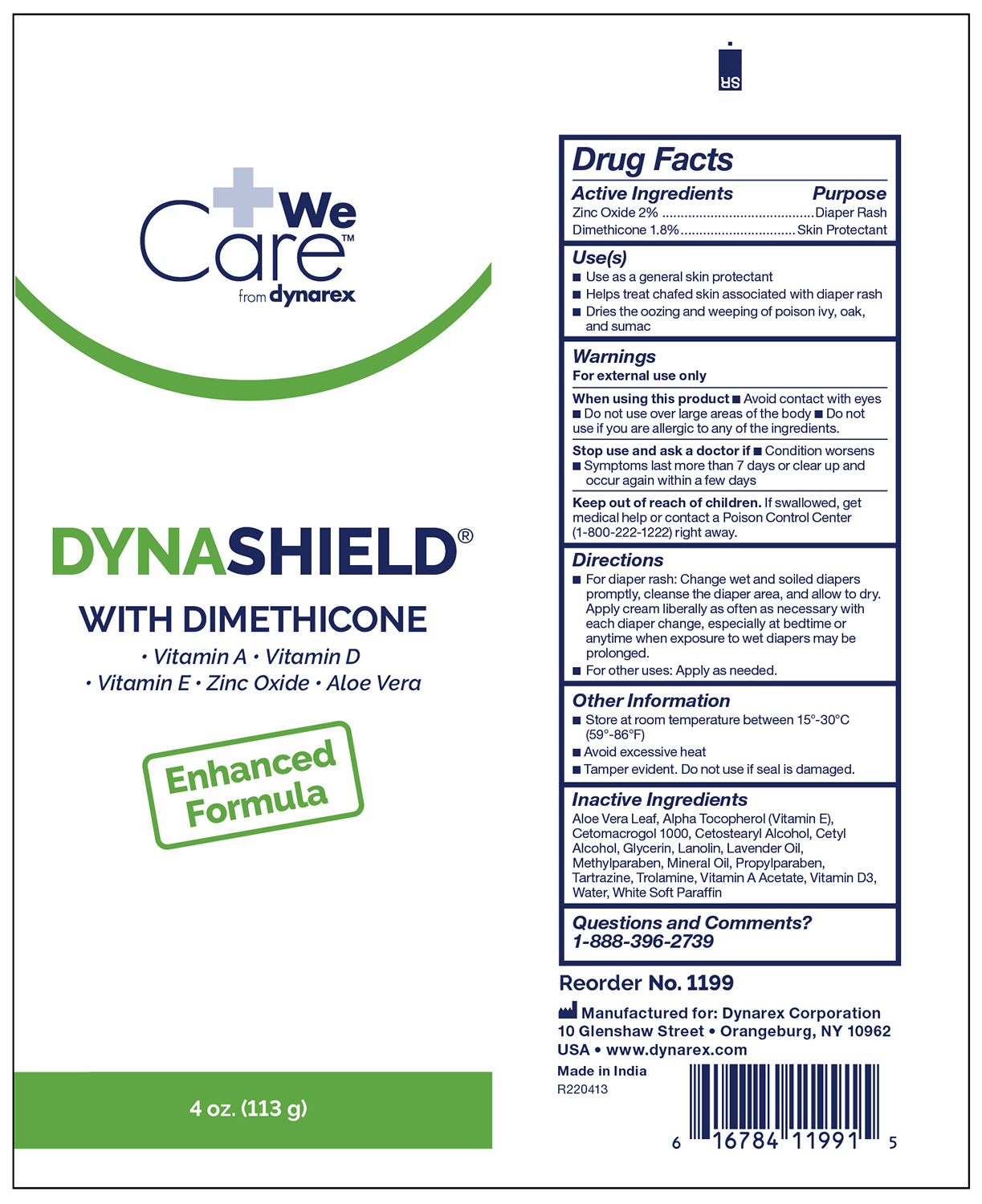 DRUG LABEL: Dynashield with Dimethicone
NDC: 67777-408 | Form: CREAM
Manufacturer: Dynarex Corporation
Category: otc | Type: HUMAN OTC DRUG LABEL
Date: 20241120

ACTIVE INGREDIENTS: DIMETHICONE 1.8 g/100 g; ZINC OXIDE 2 g/100 g
INACTIVE INGREDIENTS: WHITE PETROLATUM; METHYLPARABEN; VITAMIN A ACETATE; LAVENDER OIL; LANOLIN; CETETH-20; MINERAL OIL; PROPYLPARABEN; GLYCERIN; CETYL ALCOHOL; CETOSTEARYL ALCOHOL; CHOLECALCIFEROL; ALPHA-TOCOPHEROL; ALOE VERA LEAF; FD&C YELLOW NO. 5; TROLAMINE; WATER

1199 Dynashield with Dimethicone NDC 67777-408-03

Active Ingredients

Zinc Oxide 2%

Dimethicone 1.8%

Purpose

- Diaper rash
- Skin Protectant

Uses

• Use as a general skin protectant

• Helps treat chafed skin associated with diaper rash

• Dries the oozing and weeping of poison ivy, oak, and sumac

Warnings

For External Use Only.

When using this product:

• Avoid contact with eyes

• Do not use over large areas of the body

• So not use if you are allergic to any of the ingredients

Stop use and ask a doctor if:

- Condition worsens
- Symptoms last more than 7 days or clear up and occur again within a few days

Keep out of reach of children.

If swallowed, get medical help or contact a Poison Control Center (1-800-222-1222) right away.

Directions

• For diaper rash: Change wet and soiled diapers promptly, cleanse the diaper area, and allow to dry. Apply cream liberally as often as

necessary with each diaper change, especially at bedtime or anytime when exposure to wet diapers may be prolonged.

• For other uses: Apply as needed.

Other Information

• Store at room temperature between 15^0 - 30^0 C (59^0 - 86^0 F)

• Avoid excessive heat

• Tamper evident. Do not use if seal is damaged.

Inactive Ingredients

Aloe Vera Leaf, Alpha-Tocopherol (Vitamin E), Cetomacrogol 1000, Cetostearyl Alcohol, Cetyl Alcohol, Glycerin, Lanolin, Lavender Oil, Methylparaben, Mineral Oil, Propylparaben, Tartrazine, Trolamine, Vitamin A Acetate, Vitamin D3, Water, White Soft Paraffin

Questions and Comments?

1-888-396-2739, Monday - Friday 9AM-5PM EST

Label

DynaShield with Dimehticone